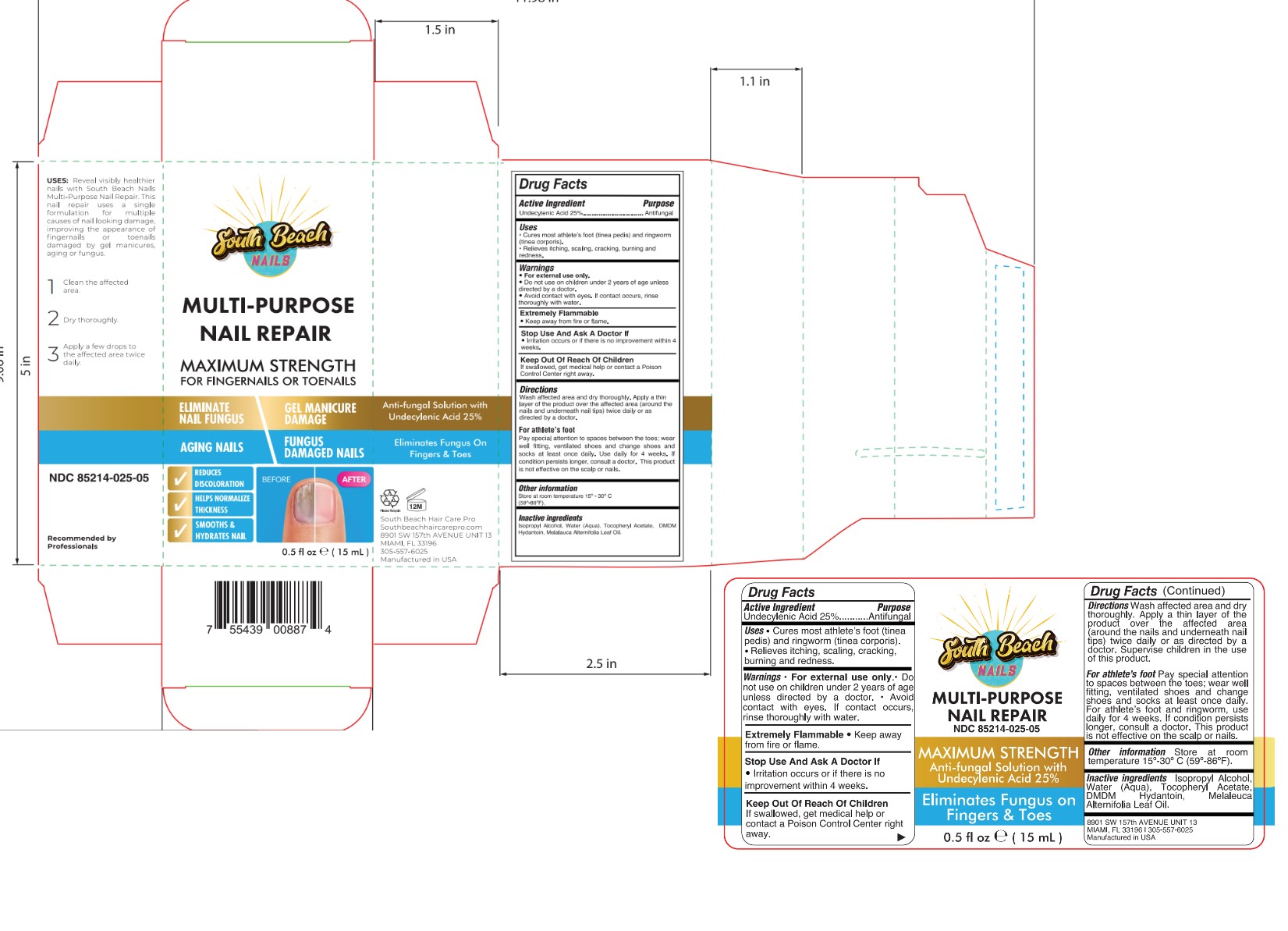 DRUG LABEL: SOUTH BEACH MULTI-PURPOSE NAIL REPAIR
NDC: 85214-025 | Form: LIQUID
Manufacturer: SOUTH BEACH HAIR CARE PROFESIONAL INC
Category: otc | Type: HUMAN OTC DRUG LABEL
Date: 20250306

ACTIVE INGREDIENTS: UNDECYLENIC ACID 25 g/100 mL
INACTIVE INGREDIENTS: DMDM HYDANTOIN; WATER; ISOPROPYL ALCOHOL; .ALPHA.-TOCOPHEROL ACETATE; MELALEUCA ALTERNIFOLIA LEAF

85214-025-05

ACTIVE INGREDIENT

Undecylenic Acid 25%

PURPOSE

Antifungal

USES:

Cures most athlete’s foot (tinea pedis) and ringworm (tinea corporis).

Relieves itching, scaling, cracking, burning, and redness.

WARNINGS

For external use only.

Do not use on children under 2 years of age unless directed by a doctor.

Avoid contact with eyes. If contact occurs, rinse thoroughly with water

EXTREMELY FLAMMABLE:

Keep away from fire or flame.

STOP USE AND ASK A DOCTOR IF

Irritation occurs or if there is no improvement within 4 weeks.

KEEP OUT OF REACH OF CHILDREN

If swallowed, get medical help or contact a Poison Control Center right away.

DIRECTIONS:

Wash affected area and dry thoroughly. Apply a thin layer of the product over the affected area (around the nails and underneath nail tips) twice daily or as directed by a doctor. Supervise children in the use of this product.

For athlete’s foot, pay special attention to spaces between the toes; wear well fitting, ventilated shoes, and change shoes and socks at least once daily. For athlete’s foot and ringworm, use daily for 4 weeks. If condition persists longer, consult a doctor. This product is not effective on the scalp or nails.

OTHER INFORMATION:

Store at room temperature 15° - 30°C (59° - 86°F)

INACTIVE INGREDIENT

Isopropyl Alcohol, Water (Aqua), Tocopheryl Acetate, DMDM Hydantoin, Melaleuca Alternifolia Leaf Oil.